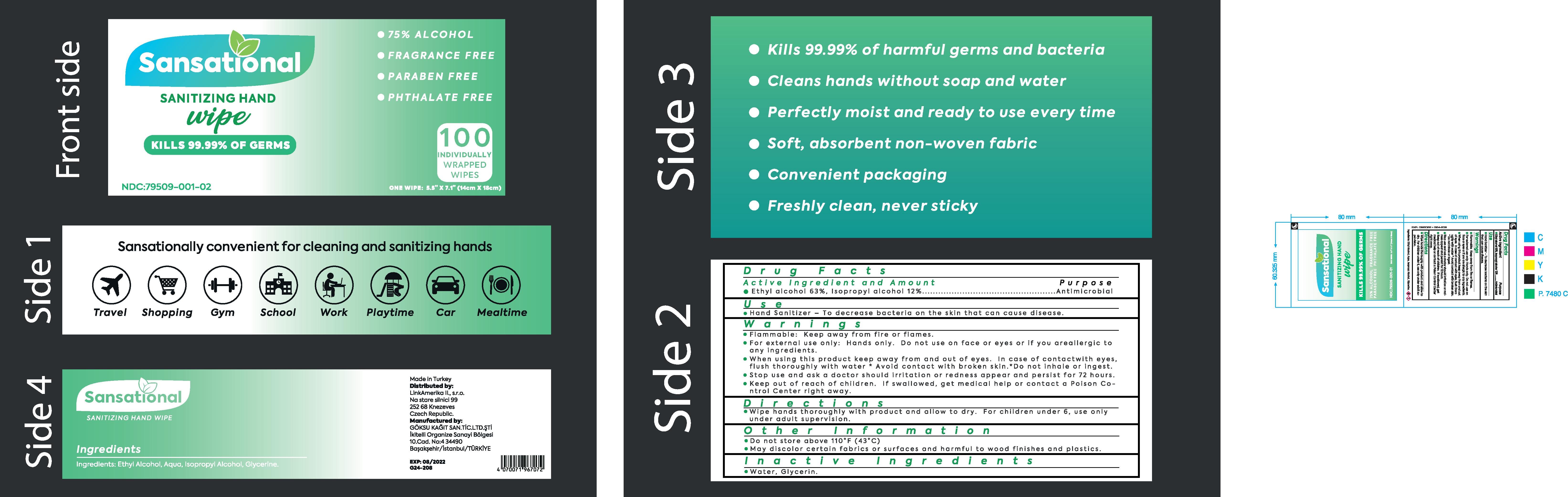 DRUG LABEL: Sansational Sanitizing Wipes
NDC: 79509-500 | Form: CLOTH
Manufacturer: GOKSU KAGIT SANAYI VE TICARET LIMITED SIRKETI
Category: otc | Type: HUMAN OTC DRUG LABEL
Date: 20200819

ACTIVE INGREDIENTS: ISOPROPYL ALCOHOL 12 U/100 U; ALCOHOL 63 U/100 U
INACTIVE INGREDIENTS: GLYCERIN; WATER

Active Ingredient(s)

Ethyl Alcohol 63% v/v. Purpose: Antimicrobial

Isopropyl Alcohol 12% v/v. Purpose: Antimicrobial

Purpose

Antimicrobial, Alcohol Wipes

Use

Alcohol Wipes to help reduce bacteria that potentially can cause disease. For use when soap and water are not available.

Warnings

For external use only. Flammable. Keep away from heat or flame

Do not use

- in children less than 2 months of age
- on open skin wounds

When using this product keep out of eyes, ears, and mouth. In case of contact with eyes, rinse eyes thoroughly with water.
Stop use and ask a doctor if irritation or rash occurs. These may be signs of a serious condition.
Keep out of reach of children. If swallowed, get medical help or contact a Poison Control Center right away.

Stop use and ask a doctor if irritation or rash occurs. These may be signs of a serious condition.

Keep out of reach of children. If swallowed, get medical help or contact a Poison Control Center right away.

Directions

- Use product on hands to cover all surfaces. Rub hands together until dry.
- Supervise children under 6 years of age when using this product to avoid swallowing.

Other information

- Store between 15-30C (59-86F)
- Avoid freezing and excessive heat above 40C (104F)

Inactive ingredients

glycerin, purified water USP

Package Label - Principal Display Panel

100 U NDC: 79509-500-01